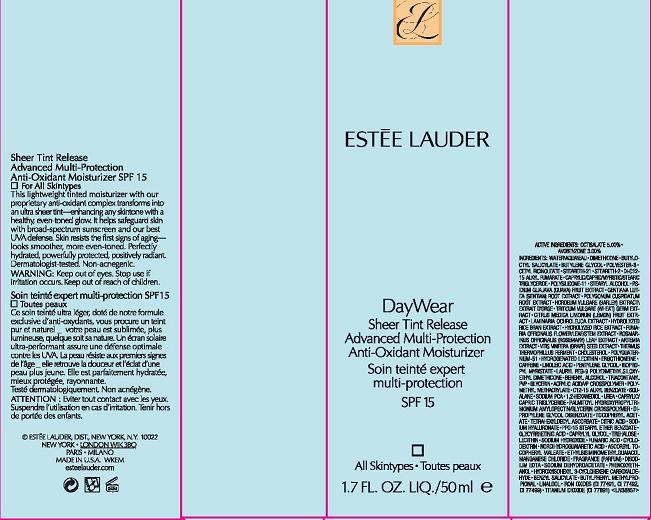 DRUG LABEL: DAYWEAR
NDC: 11559-008 | Form: LOTION
Manufacturer: ESTEE LAUDER INC
Category: otc | Type: HUMAN OTC DRUG LABEL
Date: 20101217

ACTIVE INGREDIENTS: OCTISALATE 5.0 mL/100 mL; AVOBENZONE 3.0 mL/100 mL
INACTIVE INGREDIENTS: WATER; BUTYLENE GLYCOL; DIMETHICONE; GLYCERIN; CHOLESTEROL; SQUALANE; CITRIC ACID MONOHYDRATE; LECITHIN, SOYBEAN; BUTYLATED HYDROXYTOLUENE; PHENOXYETHANOL

ACTIVE INGREDIENTS: OCTISALATE 5.00% [] AVOBENZONE 3.00%

INACTIVE INGREDIENT

INACTIVE INGREDIENTS: WATER\AQUA\EAU [] DIMETHICONE [] BUTYLOCTYL SALICYLATE [] BUTYLENE GLYCOL [] POLYESTER-8 [] CETYL RICINOLEATE [] STEARETH-21 [] STEARETH-2 [] DI-C12-15 ALKYL FUMARATE [] CAPRYLIC/CAPRIC/MYRISTIC/STEARIC TRIGLYCERIDE [] POLYSILICONE-11 [] STEARYL ALCOHOL [] PSIDIUM GUAJAVA (GUAVA) FRUIT EXTRACT [] GENTIANA LUTEA (GENTIAN) ROOT EXTRACT [] POLYGONUM CUSPIDATUM ROOT EXTRACT [] HORDEUM VULGARE (BARLEY) EXTRACT\EXTRAIT D'ORGE [] TRITICUM VULGARE (WHEAT) GERM EXTRACT [] CITRUS MEDICA LIMONUM (LEMON) FRUIT EXTRACT [] LAMINARIA OCHROLEUCA EXTRACT [] HYDROLYZED RICE BRAN EXTRACT [] HYDROLYZED RICE EXTRACT [] FUMARIA OFFICINALIS FLOWER/LEAF/STEM EXTRACT [] ROSMARINUS OFFICINALIS (ROSEMARY) LEAF EXTRACT [] ARTEMIA EXTRACT [] VITIS VINIFERA (GRAPE) SEED EXTRACT [] THERMUS THERMOPHILLUS FERMENT [] CHOLESTEROL [] POLYQUATERNIUM-51 [] HYDROGENATED LECITHIN [] ERGOTHIONEINE [] CAFFEINE [] LINOLEIC ACID [] PENTYLENE GLYCOL [] ISOPROPYL MYRISTATE [] LAURYL PEG-9 POLYDIMETHYLSILOXYETHYL DIMETHICONE [] BEHENYL ALCOHOL [] TRIACONTANYL PVP [] GLYCERIN [] ACRYLIC ACID/VP CROSSPOLYMER [] POLYMETHYL METHACRYLATE [] C12-15 ALKYL BENZOATE [] SQUALANE [] SODIUM PCA [] 1,2-HEXANEDIOL [] UREA [] CAPRYLIC/CAPRIC TRIGLYCERIDE [] PALMITOYL HYDROXYPROPYLTRIMONIUM AMYLOPECTIN/GLYCERIN CROSSPOLYMER [] DIPROPYLENE GLYCOL DIBENZOATE [] TOCOPHERYL ACETATE [] TETRAHEXYLDECYL ASCORBATE [] CITRIC ACID [] SODIUM HYALURONATE [] PPG-15 STEARYL ETHER BENZOATE [] GLYCYRRHETINIC ACID [] CAPRYLYL GLYCOL [] TREHALOSE [] LECITHIN [] SODIUM HYDROXIDE [] FUMARIC ACID [] CYCLODEXTRIN [] NORDIHYDROGUAIARETIC ACID [] ASCORBYL TOCOPHERYL MALEATE [] ETHYLBISIMINOMETHYLGUAIACOL MANGANESE CHLORIDE [] FRAGRANCE (PARFUM) [] DISODIUM EDTA [] BHT [] SODIUM DEHYDROACETATE [] PHENOXYETHANOL [] IRON OXIDES (CI 77491, CI 77492, CI 77499) [] TITANIUM DIOXIDE (CI 77891)

WARNINGS

WARNING: KEEP OUT OF EYES. DISCONTINUE USE IF IRRITATION OCCURS.

KEEP OUT OF REACH OF CHILDREN.

PACKAGE LABEL

PRINCIPAL DISPLAY PANEL:

ESTEE LAUDER
DAYWEAR
SHEER TINT RELEASE
ADVANCED MULTI-PROTECTION
ANTI-OXIDANT MOISTURIZER
SPF 15

1.7 FL OZ. LIQ/ 50ML

ESTEE LAUDER DISTR

NEW YORK, NY 10022